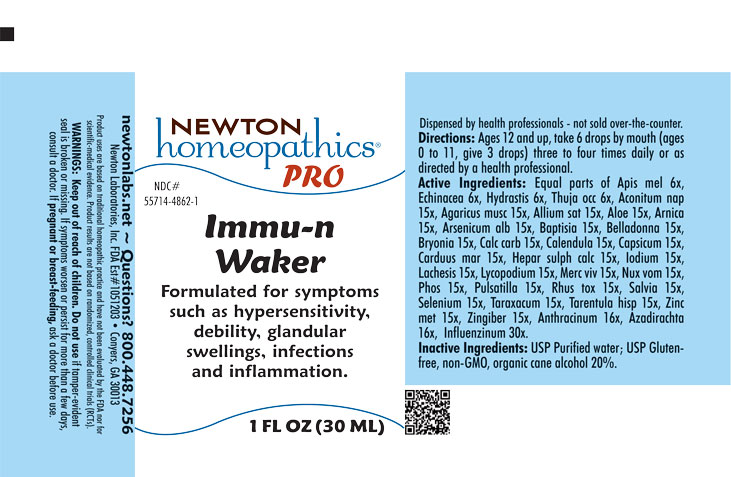 DRUG LABEL: Immu-n Waker
NDC: 55714-4862 | Form: LIQUID
Manufacturer: Newton Laboratories, Inc.
Category: homeopathic | Type: HUMAN OTC DRUG LABEL
Date: 20250521

ACTIVE INGREDIENTS: SELENIUM 15 [hp_X]/1 mL; TARAXACUM OFFICINALE 15 [hp_X]/1 mL; LYCOSA TARANTULA 15 [hp_X]/1 mL; ZINC 15 [hp_X]/1 mL; TOXICODENDRON PUBESCENS LEAF 15 [hp_X]/1 mL; ACONITUM NAPELLUS 15 [hp_X]/1 mL; INFLUENZA A VIRUS 30 [hp_X]/1 mL; APIS MELLIFERA 6 [hp_X]/1 mL; LYCOPODIUM CLAVATUM SPORE 15 [hp_X]/1 mL; GOLDENSEAL 6 [hp_X]/1 mL; THUJA OCCIDENTALIS LEAFY TWIG 6 [hp_X]/1 mL; AMANITA MUSCARIA FRUITING BODY 15 [hp_X]/1 mL; GARLIC 15 [hp_X]/1 mL; ALOE 15 [hp_X]/1 mL; ARNICA MONTANA 15 [hp_X]/1 mL; ARSENIC TRIOXIDE 15 [hp_X]/1 mL; BAPTISIA TINCTORIA ROOT 15 [hp_X]/1 mL; ATROPA BELLADONNA 15 [hp_X]/1 mL; BRYONIA ALBA ROOT 15 [hp_X]/1 mL; OYSTER SHELL CALCIUM CARBONATE, CRUDE 15 [hp_X]/1 mL; CALENDULA OFFICINALIS FLOWERING TOP 15 [hp_X]/1 mL; CAPSICUM 15 [hp_X]/1 mL; MILK THISTLE 15 [hp_X]/1 mL; CALCIUM SULFIDE 15 [hp_X]/1 mL; IODINE 15 [hp_X]/1 mL; LACHESIS MUTA VENOM 15 [hp_X]/1 mL; ECHINACEA, UNSPECIFIED 6 [hp_X]/1 mL; SAGE 15 [hp_X]/1 mL; INFLUENZA B VIRUS 30 [hp_X]/1 mL; ANEMONE PULSATILLA 15 [hp_X]/1 mL; AZADIRACHTA INDICA BARK 16 [hp_X]/1 mL; MERCURY 15 [hp_X]/1 mL; STRYCHNOS NUX-VOMICA SEED 15 [hp_X]/1 mL; GINGER 15 [hp_X]/1 mL; PHOSPHORUS 15 [hp_X]/1 mL; BACILLUS ANTHRACIS IMMUNOSERUM RABBIT 16 [hp_X]/1 mL
INACTIVE INGREDIENTS: WATER; ALCOHOL

Immu-n Waker 4862L

INDICATIONS & USAGE SECTION

Formulated for symptoms such as hypersensitivity, debility, glandular swellings, infections and inflammation.

DOSAGE & ADMINISTRATION SECTION

Directions: Ages 12 and up, take 6 drops by mouth (ages 0 to 11, give 3 drops) three to four times daily or as directed by a health professional.

OTC - ACTIVE INGREDIENT SECTION

Equal parts of Apis mel 6x, Echinacea 6x, Hydrastis 6x, Thuja occ 6x, Aconitum nap 15x, Agaricus musc 15x, Allium sat 15x, Aloe 15x, Arnica 15x, Arsenicum alb 15x, Baptisia 15x, Belladonna 15x, Bryonia 15x, Calc carb 15x, Calendula 15x, Capsicum 15x, Carduus mar 15x, Hepar sulph calc 15x, Iodium 15x, Lachesis 15x, Lycopodium 15x, Merc viv 15x, Nux vom 15x, Phos 15x, Pulsatilla 15x, Rhus tox 15x, Salvia 15x, Selenium 15x, Taraxacum 15x, Tarentula hisp 15x, Zinc met 15x, Zingiber 15x, Anthracinum 16x, Azadirachta 16x, Influenzinum 30x.

OTC - PURPOSE SECTION

Formulated for symptoms such as hypersensitivity, debility, glandular swellings, infections and inflammation.

INACTIVE INGREDIENT SECTION

Inactive Ingredients: USP Purified Water; USP Gluten-free, non-GMO, organic cane alcohol 20%.

QUESTIONS SECTION

newtonlabs.net - Questions? 800.448.7256

Newton Laboratories, Inc. FDA Est # 1051203 Conyers, GA 30013

WARNINGS SECTION

WARNINGS: Keep out of reach of children. Do not use if tamper-evident seal is broken or missing. If symptoms worsen or persist for more than a few days, consult a doctor. If pregnant or breast-feeding, ask a doctor before use.

OTC - PREGNANCY OR BREAST FEEDING SECTION

If pregnant or breast-feeding, ask a doctor before use.

OTC - KEEP OUT OF REACH OF CHILDREN SECTION

Keep out of reach of children.